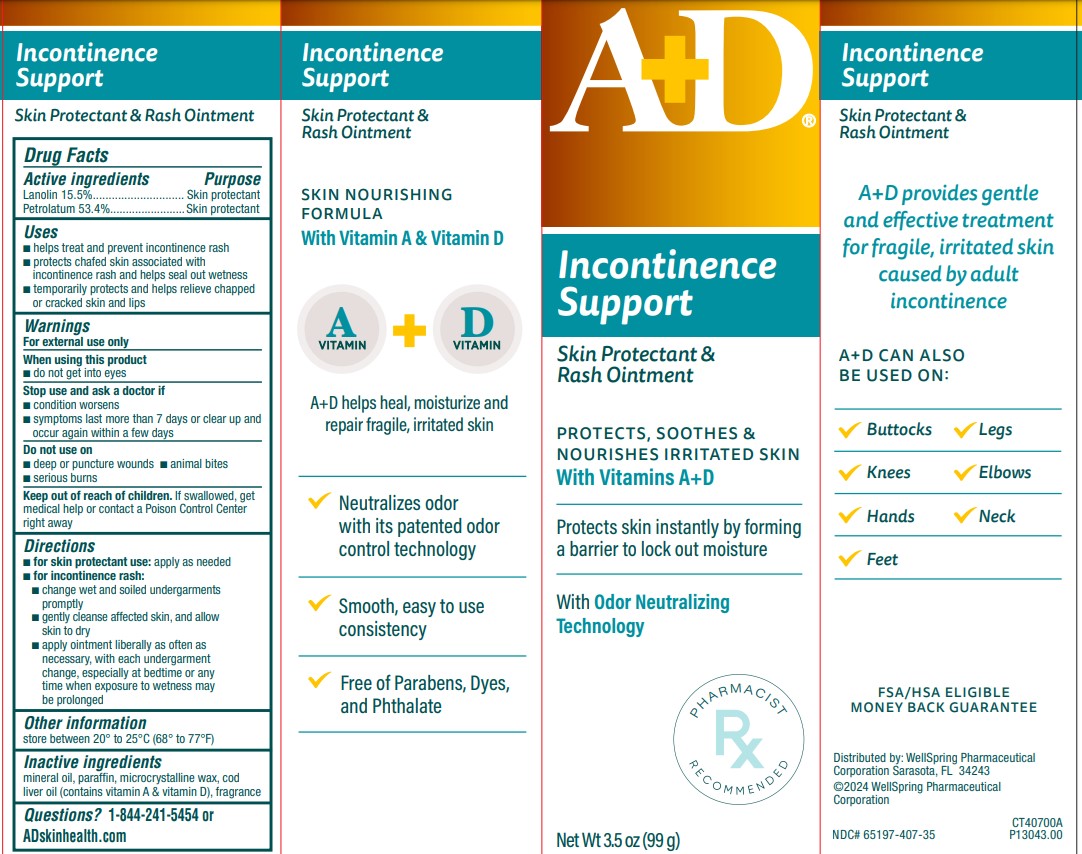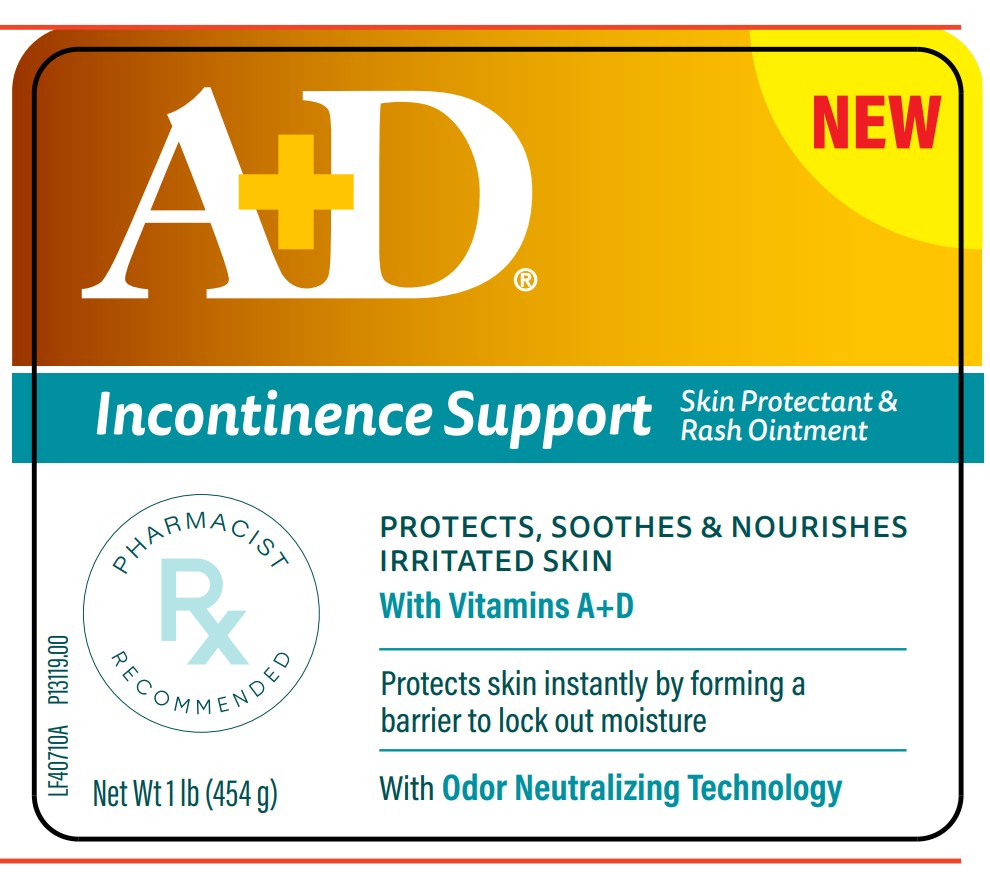 DRUG LABEL: AD Incontinence Support
NDC: 65197-407 | Form: OINTMENT
Manufacturer: WellSpring Pharmaceutical Corporation
Category: otc | Type: HUMAN OTC DRUG LABEL
Date: 20250307

ACTIVE INGREDIENTS: LANOLIN 15.5 g/100 g; PETROLATUM 53.4 g/100 g
INACTIVE INGREDIENTS: MINERAL OIL; PARAFFIN; MICROCRYSTALLINE WAX; COD LIVER OIL

A+D Incontinence Support Ointment 3.5oz and 1lb

Active Ingredients

Lanolin 15.5%

Petrolatum 53.4%

Purpose

Skin protectant

Skin protectant

Uses

- helps treat and prevent incontinence rash
- protects chafed skin associated with incontinence rash and helps seal out wetness
- temporarily protects and helps relieve chapped or cracked skin and lips

Warnings

For external use only

When using this product

- do not get into eyes

Stop use and ask a doctor if

- condition worsens
- symptoms last more than 7 days or clear up and occur again within a few days

Do not use on

- deep or puncture wounds
- animal bites
- serious burns

Keep out of reach of children

- If swallowed, get medical help or contact a Poison Control Center right away.

Directions

- for skin protectant use: apply as needed
- for incontinence rash:
  - change wet and soiled undergarments promptly
  - gently cleanse affected skin, and allow skin to dry
  - apply ointment liberally as often as necessary, with each undergarment change, especially at bedtime or any time when exposure to wetness may be prolonged

Other information

store between 20° to 25°C (68° to 77°F)

Inactive ingredients

mineral oil, paraffin, microcrystalline wax, cod liver oil (contains vitamin A & vitamin D), fragrance

Questions?

1-844-241-5454 or ADskinhealth.com

Distributed by:

WellSpring Pharmaceutical Corporation
Sarasota, FL 34243

© 2024 WellSpring Pharmaceutical Corporation

PACKAGE LABEL. PRINCIPAL DISPLAY PANEL

A+D Incontinence Support Ointment 3.5oz

Skin Protectant & Rash Ointment

PROTECTS, SOOTHES & NOURISHES IRRITATED SKIN with Vitamins A+D

Protects skin instantly by forming a barrier to lock out moisture

With Odor Neutralizing Technology

PHARMACIST RECOMMENDED

NET WT 3.5oz (99g)

CT40700A

NDC# 65197-407-35

P13043.00

CT40700A A+D Incontinence Support Ointment 3.5oz

A+D Incontinence Support Ointment 1lb

Skin Protectant & Rash Ointment

PROTECTS, SOOTHES & NOURISHES IRRITATED SKIN with Vitamins A+D

Protects skin instantly by forming a barrier to lock out moisture

With Odor Neutralizing Technology

PHARMACIST RECOMMENDED

NET WT 16 lb (454g)

LF40710A

NDC# 65197-407-16

P13119.00

A+D Incontinence Support Ointment 1 lb